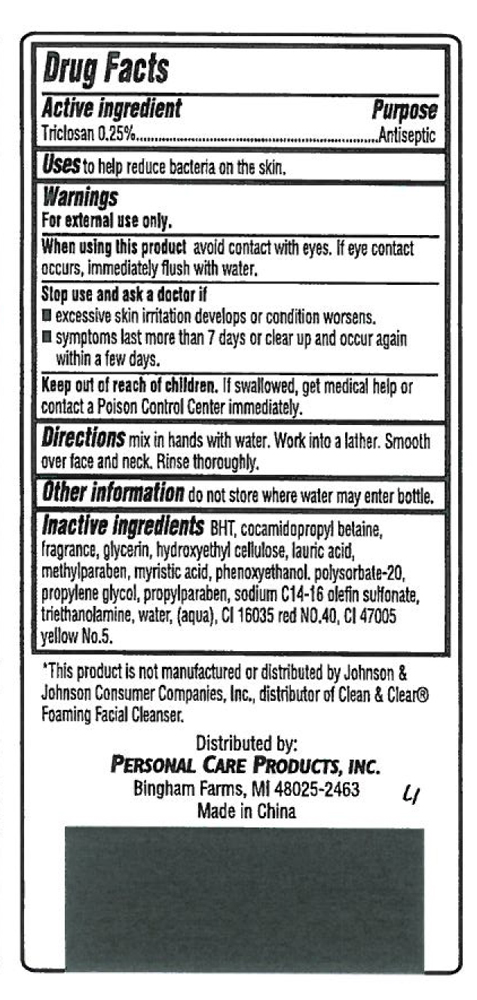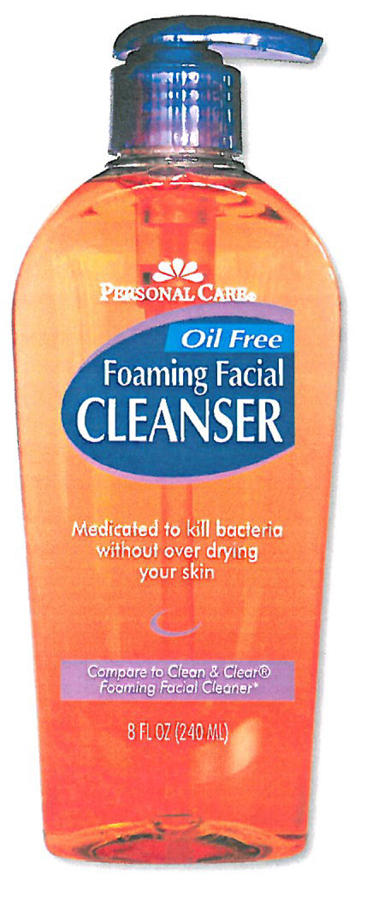 DRUG LABEL: Oil Free Foaming Facial Cleanser
NDC: 29500-0241 | Form: LIQUID
Manufacturer: Personal Care Products, Inc.
Category: otc | Type: HUMAN OTC DRUG LABEL
Date: 20100601

ACTIVE INGREDIENTS: TRICLOSAN 0.25 mL/100 mL
INACTIVE INGREDIENTS: BUTYLATED HYDROXYTOLUENE; COCAMIDOPROPYL BETAINE; GLYCERIN; LAURAMIDE; METHYLPARABEN; MYRISTIC ACID; PHENOXYETHANOL; POLYSORBATE 20; PROPYLENE GLYCOL; PROPYLPARABEN; SODIUM C14-16 OLEFIN SULFONATE; TROLAMINE

Personal Care Oil Free Foaming Facial Cleanser

Drug Facts

Active Ingredient Purpose

Triclosan (0.25%).....................Antiseptic

PURPOSE

Uses: to help reduce bacteria on the skin.

Warnings

For external use only.

When using this product avoid contact with eyes. if eye contact occurs, immediately flush with water.

Stop use and ask a doctor if

excessive skin irritation develops or condition worsens

symptoms last more than 7 days or clear up and occur again within a few days.

Keep out of reach of children. if swallowed, get medical help or contact a Poison Control Center immediately.

DOSAGE AND ADMINISTRATION

Enter section text here

Other information: Do not store where water may enter bottle.

Inactive Ingredients

BHT, cocamidopropyl betaine, fragrance, glycerin, hydroxyethyl cellulose, lauric acid, methylparaben, myfistic acid, phenoxyethanol, polysorbate-20, propylene glycol, propylparaben, sodium C14-16 olefin sulfonate, triethanolamine, water (aqua), CI 16035 red NO 40, CI 47005 yellow No. 5

*This product is not manufactured or distributed by Johnson and Johnson Consumer companies, Inc. distributor of Clean and Clear Foaming Facial Cleanser

Distributed by Personal Care Products, Inc.

Bingham Farms, MI 48025-2463

Made in China

PACKAGE LABEL

Personal Care Oil Free

Foaming Facial Cleanser

Medicated to kill bacteria

without over drying your skin

Compare to Clean and Clear Foaming Facial Cleaner

8 FL OZ (240 ML)